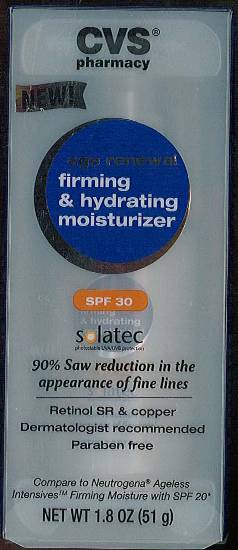 DRUG LABEL: age renewal firming and hydrating moisturizer
NDC: 59779-301 | Form: CREAM
Manufacturer: Woonsocket Prescription Center, Incorporated
Category: otc | Type: HUMAN OTC DRUG LABEL
Date: 20111111

ACTIVE INGREDIENTS: Octinoxate 0.075 g/1 g; Octisalate 0.05 g/1 g; Oxybenzone 0.04 g/1 g; Zinc Oxide 0.02 g/1 g
INACTIVE INGREDIENTS: water; glycerin; glyceryl monostearate; isopropyl myristate; cetostearyl alcohol; squalane; phenoxyethanol; retinol; polysorbate 20; arginine; soybean; .alpha.-tocopherol acetate, DL-; Picea abies wood; SODIUM POLYACRYLATE (8000 MW); cetearyl glucoside; bentonite; xanthan gum; sorbitol; sodium borate; sodium hydroxide; methylparaben; ethylhexylglycerin; butylated hydroxytoluene; ascorbic acid; edetate disodium; panthenol; titanium dioxide

age renewal firming and hydrating moisturizer

ACTIVE INGREDIENT

Active Ingredients: Octinoxate 7.5%, Octisalate 5%, Oxybenzone 4%, Zinc Oxide 2%

GENERAL PRECAUTIONS

Caution: For external use only. Avoid getting into eyes. If product gets into eyes, rinse thoroughly with water. In the beginning you may experience mild tingling, warming, flaking and/or redness. This is a sign that the product is working. If discomfort occurs reduce use to every other day until your skin adjusts. Discontinue use if irritation occurs.

Discontinue use if irritation occurs.